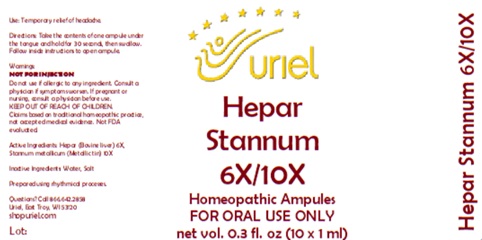 DRUG LABEL: Hepar Stannum 6/10
NDC: 48951-5047 | Form: LIQUID
Manufacturer: Uriel Pharmacy Inc.
Category: homeopathic | Type: HUMAN OTC DRUG LABEL
Date: 20260203

ACTIVE INGREDIENTS: MAMMAL LIVER 6 [hp_X]/1 mL; TIN 10 [hp_X]/1 mL
INACTIVE INGREDIENTS: WATER; SODIUM CHLORIDE

Hepar Stannum 6/10

PURPOSE

Use: Temporary relief of headache.

INDICATIONS AND USAGE

FOR ORAL USE ONLY

DOSAGE AND ADMINISTRATION

Directions: Take the contents of one ampule under the tongue and hold for 30 seconds, then swallow. Follow inside instructions to open ampule.

Warnings:
NOT FOR INJECTION
Do not use if allergic to any ingredient. Consult a physician if symptoms worsen. If pregnant or nursing, consult a physician before use.
Claims based on traditional homeopathic practice, not accepted medical evidence. Not FDA evaluated

KEEP OUT OF REACH OF CHILDREN.

Active Ingredients: Hepar (Bovine liver)6X,
Stannum metallicum (Metallic tin) 10X

Inactive Ingredients: Water, Salt

Prepared using rhythmical processes.

Questions? Call 866.642.2858
Uriel, East Troy, WI 53120
shopuriel.com Lot: